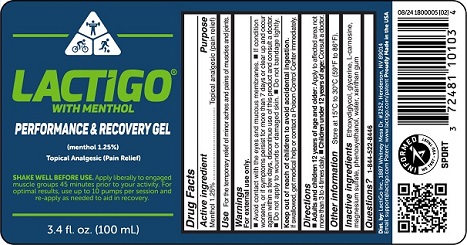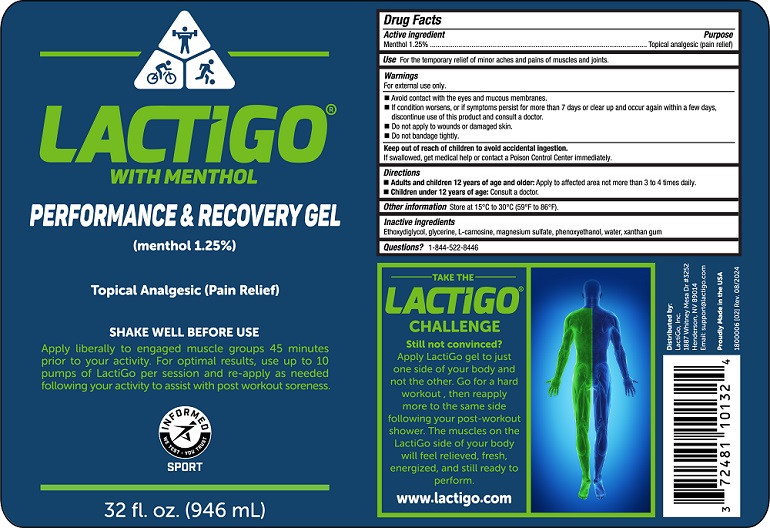 DRUG LABEL: LactiGo
NDC: 72481-101 | Form: GEL
Manufacturer: LactiGo, Inc.
Category: otc | Type: HUMAN OTC DRUG LABEL
Date: 20240903

ACTIVE INGREDIENTS: MENTHOL, UNSPECIFIED FORM 12.5 mg/1 mL
INACTIVE INGREDIENTS: MAGNESIUM SULFATE ANHYDROUS; DIETHYLENE GLYCOL MONOETHYL ETHER; WATER; CARNOSINE; XANTHAN GUM; PHENOXYETHANOL; GLYCERIN

LactiGo with Menthol Performance & Recovery Gel

Active ingredient

Menthol 1.25%

Purpose

Topical analgesic

Use

For the temporary relief of minor aches and pains of muscles and joints.

Warnings

For external use only.

- Avoid contact with eyes and mucous membranes.
- If contention worsens, or if symptoms persist for more than 7 days or clear up and occur again within a few days, discontinue use of this product and consult a doctor.
- Do not apply to wounds or damaged skin.
- Do not bandage tightly.

Keep out of reach of children to avoid accidental ingestion.

If swallowed, get medical help or contact a Poison Control Center immediately.

Directions

Adults and children 2 years of age and older: Apply to affected area not more than 3 to 4 times daily.

Children under 2 years of age: Consult a doctor.

Other information

Store at 15°C to 30°C (59°F to 86°F).

Inactive ingredients

Ethoxydiglycol, glycerine, L-carnosine, magnesium sulfate, phenoxyethanol, water, xanthan gum

Questions?

1-844-522-8446